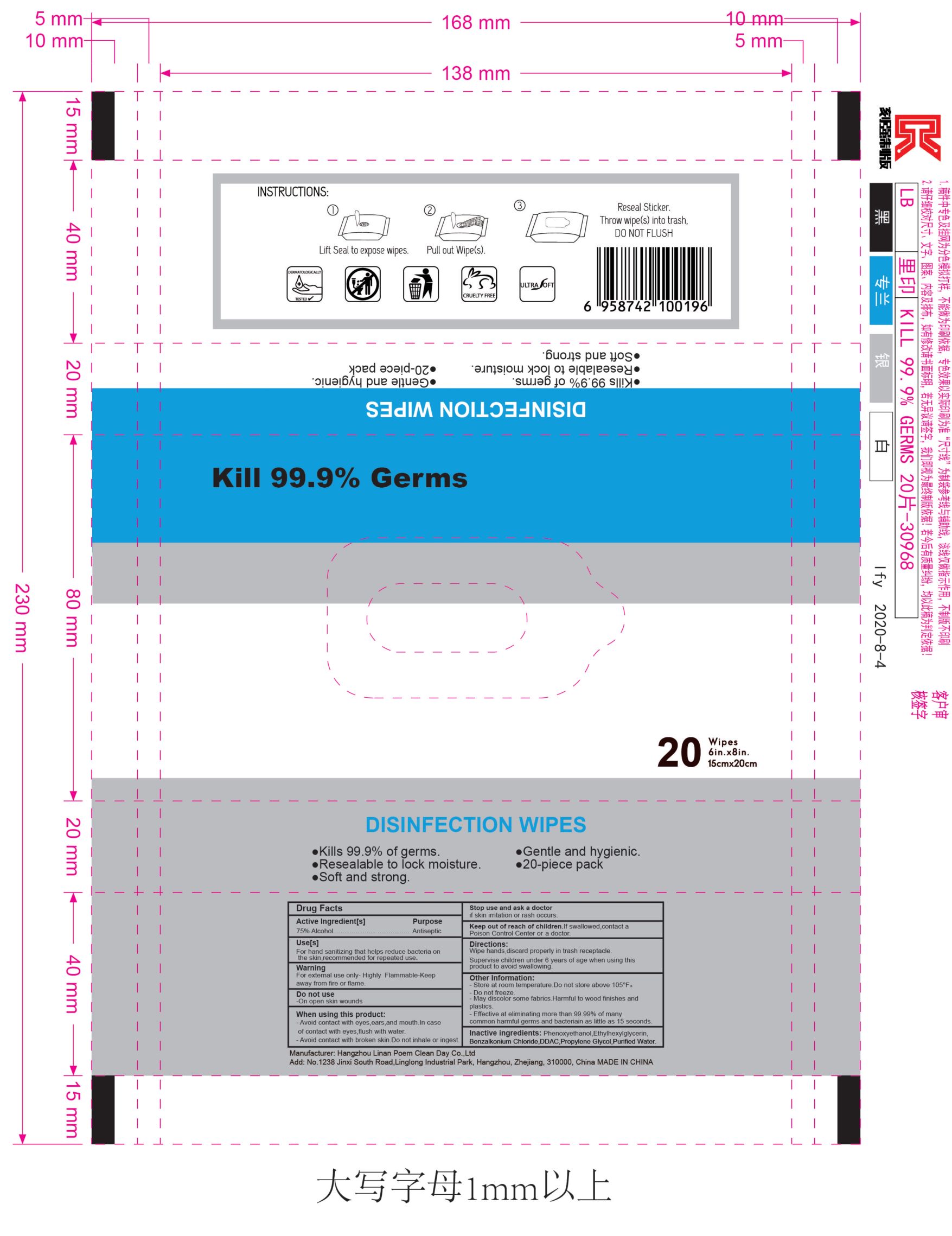 DRUG LABEL: DISINFECTION WIPES
NDC: 56076-005 | Form: CLOTH
Manufacturer: Hangzhou Linan Poem Clean Day Co., Ltd.
Category: otc | Type: HUMAN OTC DRUG LABEL
Date: 20200806

ACTIVE INGREDIENTS: ALCOHOL 75 mL/100 mL
INACTIVE INGREDIENTS: PHENOXYETHANOL; ETHYLHEXYLGLYCERIN; WATER; PROPYLENE GLYCOL; BENZALKONIUM CHLORIDE; DIDECYLDIMONIUM CHLORIDE

DISINFECTION WIPES
20PCS
56076-005-01

Active Ingredient(s)

75% Alcohol

Purpose

Antiseptic

Use

For hand sanitizing that helps reduce bacteria on the skin, recommended for repeated use.

Warnings

- For external use only
- Highly Flammable-Keep away from fire or flame.

Do not use

On open skin wounds

WHEN USING

- Avoid contact with eyes, ears, and mouth. ln case of contact with eyes, flush with water.
- Avoid contact with broken skin.
- Do not inhale or ingest.

STOP USE

Stop using and ask a doctor if irritation or rash occurs.

Keep out of reach of children. If swallowed, contact a Poison Control Center or a doctor.

Directions

- Wipe hands, discard properly in trash receptacle.
- Supervise children under 6 years of age when using this product to avoid swallowing.

Other information

- Store at room temperature. Do not store above 105℉.
- Do not freeze.
- May discolor some fabrics. Harmful to wood finishes and plastics.
- Effective at eliminating more than 99.99% of many common harmful germs and bacteriain as little as 15 seconds.

Inactive ingredients

Phenoxyethanol, Ethylhexylglycerin, Benzalkonium Chloride, DDAC, Propylene Glycol, Purified Water.

Package Label - Principal Display Panel

20 wipes NDC: 56076-005-01